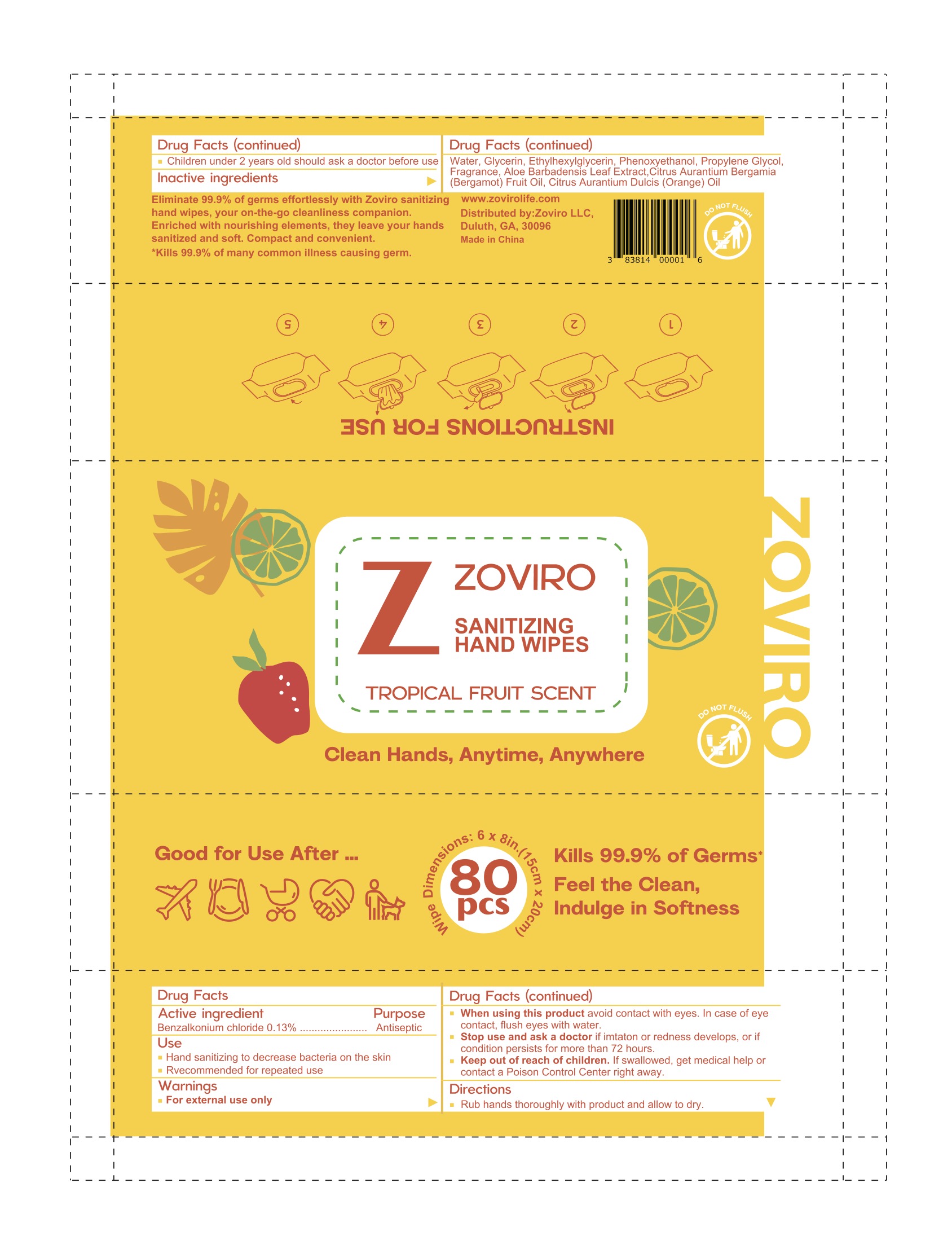 DRUG LABEL: Zoviro
NDC: 83814-004 | Form: SWAB
Manufacturer: Zoviro, LLC
Category: otc | Type: HUMAN OTC DRUG LABEL
Date: 20250807

ACTIVE INGREDIENTS: BENZALKONIUM CHLORIDE 0.13 g/100 g
INACTIVE INGREDIENTS: ETHYLHEXYLGLYCERIN; GLYCERIN; PHENOXYETHANOL; WATER; BERGAMOT OIL; PROPYLENE GLYCOL; ORANGE OIL; ALOE VERA LEAF

Zoviro Alcohol-Free Hand Sanitizing Wipes Tropical Fruit

Active ingredient

Benzalkonium chloride 0.13%

Purpose

Antiseptic

When using this product avoid contact with eyes. In case of eye contact, flush eyes with water.

Stop use and ask a doctor if imtaton or redness develops, or if condition persists for more than 72 hours.

Keep out of reach of children. If swallowed, get medical help or contact a Poison Control Center right away.

Inactive ingredients

Water, Glycerin, Ethylhexylglycerin, Phenoxyethanol, Propylene Glycol, Fragrance, Aloe Barbadensis Leaf Extract,Citrus Aurantium Bergamia (Bergamot) Fruit Oil, Citrus Aurantium Dulcis (Orange) Oil

Directions

Rub hands thoroughly with product and allow to dry.

Children under 2 years old should ask a doctor before use.

Use

Hand sanitizing to decrease bacteria on the skin

Recommended for repeated use

Warnings

For external use only